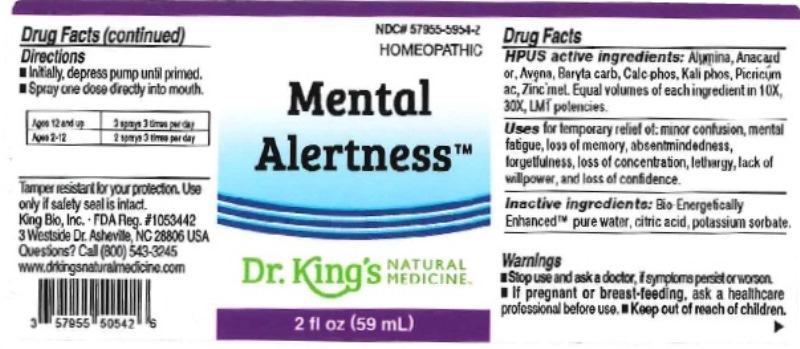 DRUG LABEL: Mental Alertness
NDC: 57955-5954 | Form: LIQUID
Manufacturer: King Bio Inc.
Category: homeopathic | Type: HUMAN OTC DRUG LABEL
Date: 20160323

ACTIVE INGREDIENTS: ALUMINUM OXIDE 10 [hp_X]/59 mL; SEMECARPUS ANACARDIUM JUICE 10 [hp_X]/59 mL; AVENA SATIVA FLOWERING TOP 10 [hp_X]/59 mL; BARIUM CARBONATE 10 [hp_X]/59 mL; TRIBASIC CALCIUM PHOSPHATE 10 [hp_X]/59 mL; POTASSIUM PHOSPHATE, DIBASIC 10 [hp_X]/59 mL; PICRIC ACID 10 [hp_X]/59 mL; ZINC 10 [hp_X]/59 mL
INACTIVE INGREDIENTS: WATER; ANHYDROUS CITRIC ACID; POTASSIUM SORBATE

Mental Alertness™

ACTIVE INGREDIENT

Drug Facts__________________________________________________________________________________________________________

HPUS active ingredients: Alumina, Anacardium orientale, Avena sativa, Baryta carbonica, Calcarea phosphorica, Kali phosphoricum, Picricum acidum, Zincum metallicum. Equal volumes of each ingredient in 10X, 30X, and LM1 potencies.

INDICATIONS AND USAGE

Uses for temporary relief of: minor confusion, mental fatigue, loss of memory, absentmindedness, forgetfulness, loss of concentration, lethargy, lack of willpower, and loss of confidence.

Inactive Ingredients:

Bio-Energetically Enhanced™ pure water, citric acid and potassium sorbate.

Warnings

- Stop use and ask a doctor if symptoms persist or worsen.
- If pregnant or breast-feeding, ask a healthcare professional before ues.

- Keep out of reach of children.

Directions

- Initially, depress pump until primed.
- Spray one dose directly into mouth.
- Ages 12 and up: 3 sprays 3 times per day.
- Ages 2-12: 2 sprays 3 times per day.

OTHER SAFETY INFORMATION

Tamper resistant for your protection. Use only if safety seal is intact.

PURPOSE

Uses for temporary relief of:

- minor confusion
- mental fatigue
- loss of memory
- absentmindedness
- forgetfulness
- loss of concentration
- lethargy
- lack of willpower
- loss of confidence